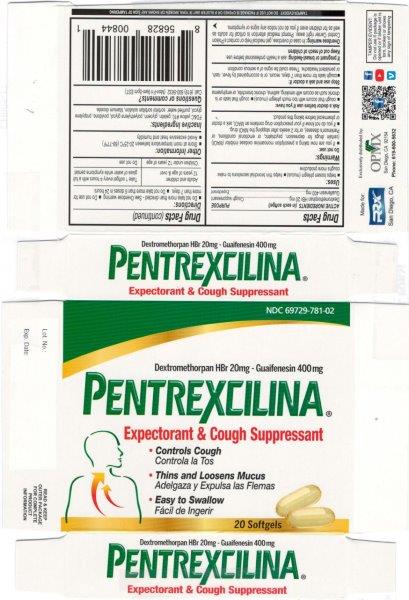 DRUG LABEL: DEXTROMETHORPHAN HBR, GUAIFENESIN
NDC: 69729-781 | Form: CAPSULE, LIQUID FILLED
Manufacturer: OPMX LLC
Category: otc | Type: HUMAN OTC DRUG LABEL
Date: 20240405

ACTIVE INGREDIENTS: DEXTROMETHORPHAN HYDROBROMIDE 20 mg/1 1; GUAIFENESIN 400 mg/1 1
INACTIVE INGREDIENTS: WATER; D&C YELLOW NO. 10; PROPYLENE GLYCOL; SORBITOL; POLYETHYLENE GLYCOL 400; GLYCERIN; GELATIN; POVIDONE K30; SODIUM HYDROXIDE; SORBITAN

Pentrexcilina Expectorant & Cough Suppressant

ACTIVE INGREDIENT

Dextromethorphan HBr 20mg

Guaifenesin 400mg

PURPOSE

Cough suppressant

Expectorant

INACTIVE INGREDIENT

FD&C yellow #10, gelatin, glycerin, polyethylene glycol, povidone, propylene glycol, purified water, sorbitol sorbitan solution, titanium dioxide.

DOSAGE AND ADMINISTRATION

Do not take more than directed – See overdose warning
Do not use for more than 7 days
Do not take more than 6 doses in 24 hours

Adults and children 12 years of age and over: take 1 softgel every 4 hours with a full glass of water while symptoms persist

Children under 12 years of age: do not use

INDICATIONS AND USAGE

Helps loosen phlegm (mucus)
Helps thin bronchial secretions to make coughs more productive

Do not use:

- If you are now taking a prescription monoamine oxidase inhibitor (MAOI) (certain drugs for depression, psychiatric, or emotional conditions, or Parkinson’s disease), or for 2 weeks after stopping the MAOI drug.
- If you do not know if your prescription drug contains an MAOI, ask a doctor or pharmacist before taking this product.

Ask a doctor before use if you have:

- Cough that occurs with too much phlegm (mucus)
- Cough that lasts or is chronic such as occurs with smoking, asthma, chronic bronchitis, or emphysema

Stop use and ask a doctor if:

Cough lasts for more than 7 days, recurs, or is accompanied by fever, rash, or persistent headache. These could be signs of a serious condition

If pregnant or breast-feeding: ask a health professional before use.

Keep out of reach of children.

Keep out of reach of children

OVERDOSAGE

OVERDOSE WARNING: In case of overdose, get medical help or contact a Poison Control Center right away. Prompt medical attention is critical for adults as well as for children even if you do not notice any signs or symptoms.

OTHER SAFETY INFORMATION

store at room temperature between 20-25°C (68-77ºF)

avoid excessive heat and humidity